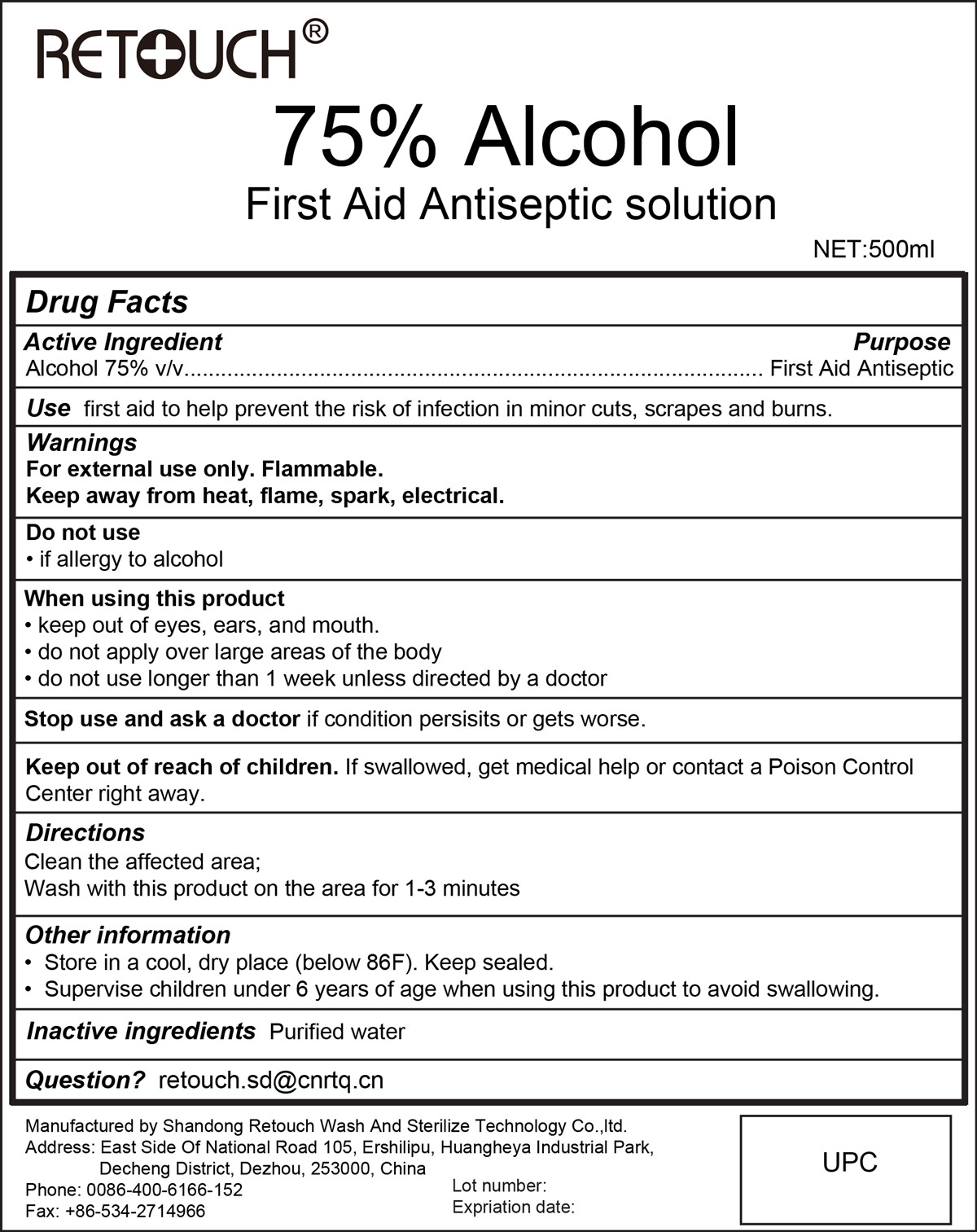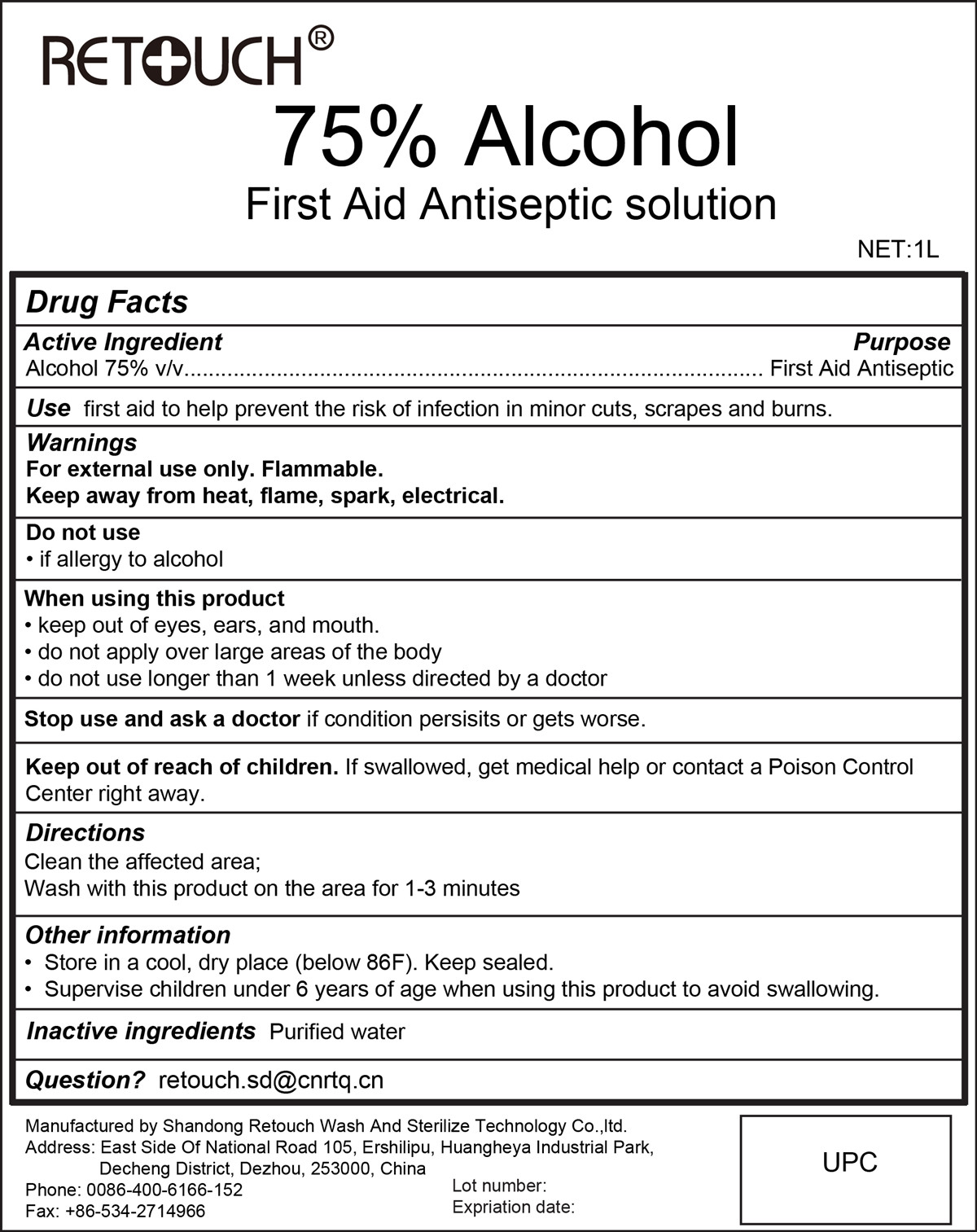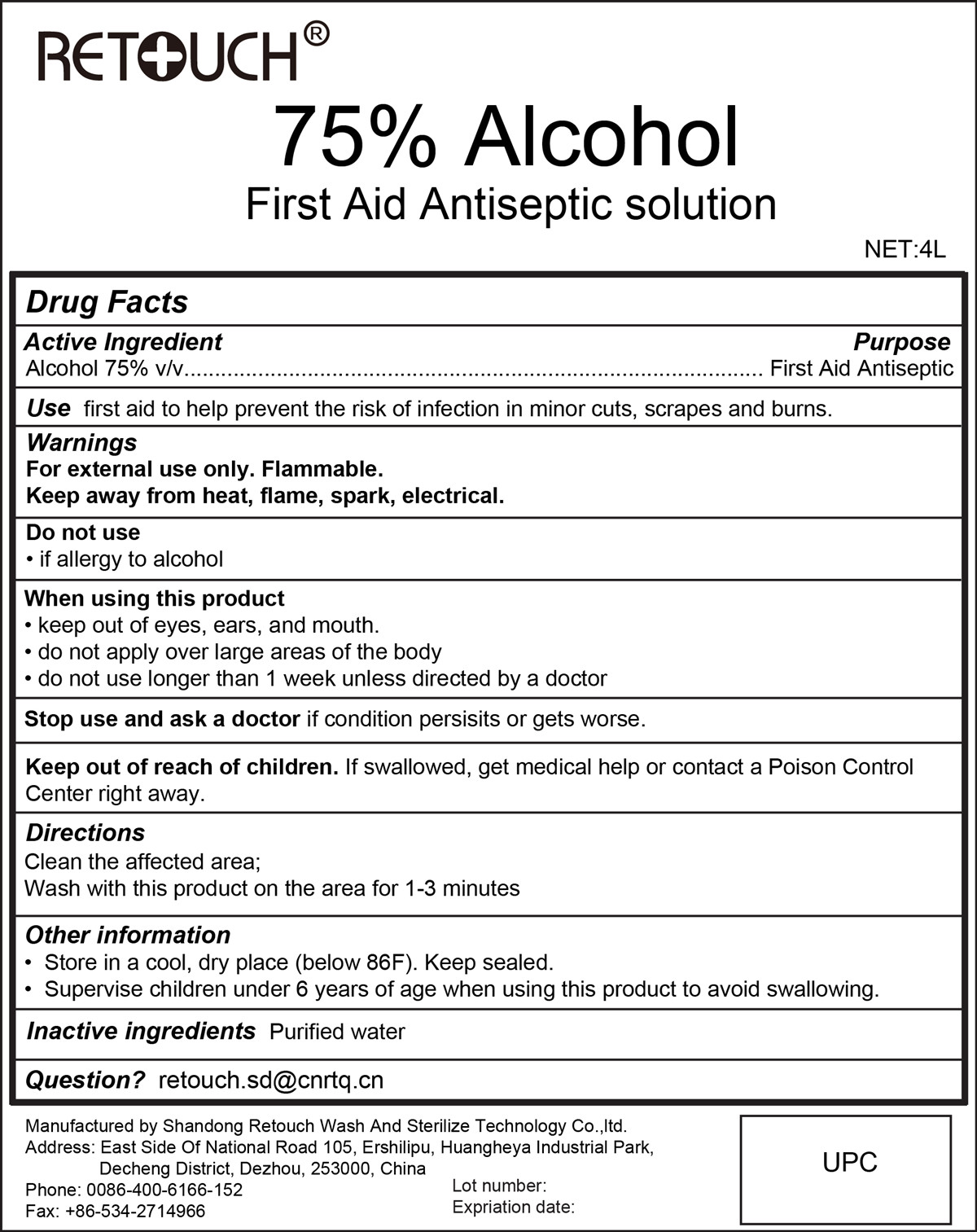 DRUG LABEL: 75% Alcohol
NDC: 75532-002 | Form: LIQUID
Manufacturer: Shandong Retouch Wash And Sterilize Technology Co.,ltd.
Category: otc | Type: HUMAN OTC DRUG LABEL
Date: 20230210

ACTIVE INGREDIENTS: ALCOHOL 75 mL/100 mL
INACTIVE INGREDIENTS: WATER

75% Alcohol

Active Ingredient(s)

Alcohol 75% v/v. Purpose: First Aid Antiseptic

Purpose

First Aid Antiseptic

Use

first aid to help prevent the risk of infection in minor cuts, scrapes and burns

Warnings

For external use only. Flammable.

Keep away from heat, flame, spark, electrical.

Do not use

if allergy to alcohol

When using this product

keep out of eyes, ears, and mouth.

do not apply over large areas of the body.

do not use longer than 1 week unless directed by a doctor.

Stop use and ask a doctor if condition persists or gets worse.

Keep out of reach of children. If swallowed, get medical help or contact a Poison Control Center right away.

Directions

Clean the affected area

Wash with this product on the area for 1-3 minutes

Other information

Store in a cool, dry place (below 86F). Keep sealed.

Supervises children under 6 years of age when using this product to avoid swallowing.

Inactive ingredients

purified water

Package Label - Principal Display Panel

500 mL NDC:75532-002-01

75532-002-01 1000ml

75532-002-03 4000ml